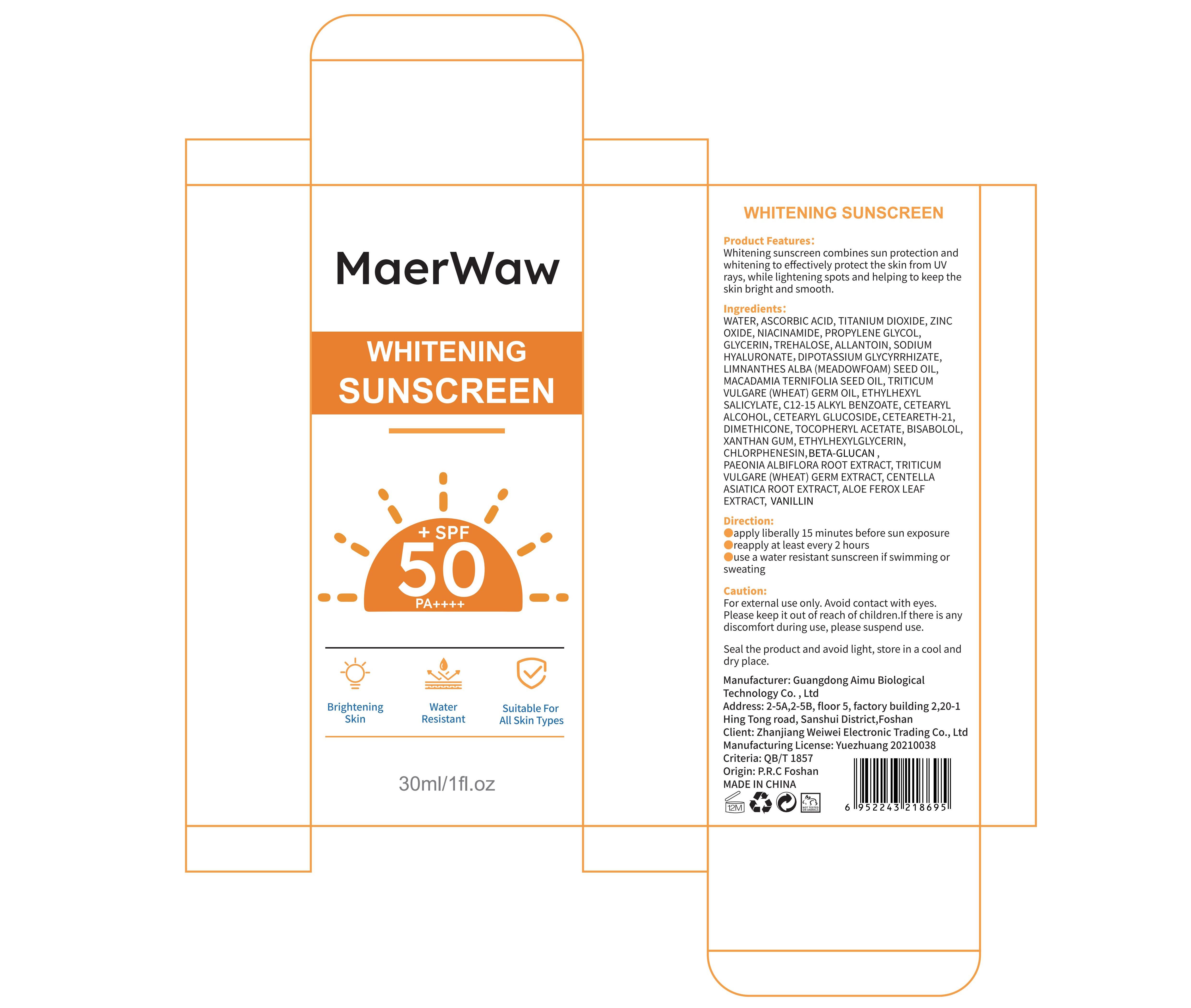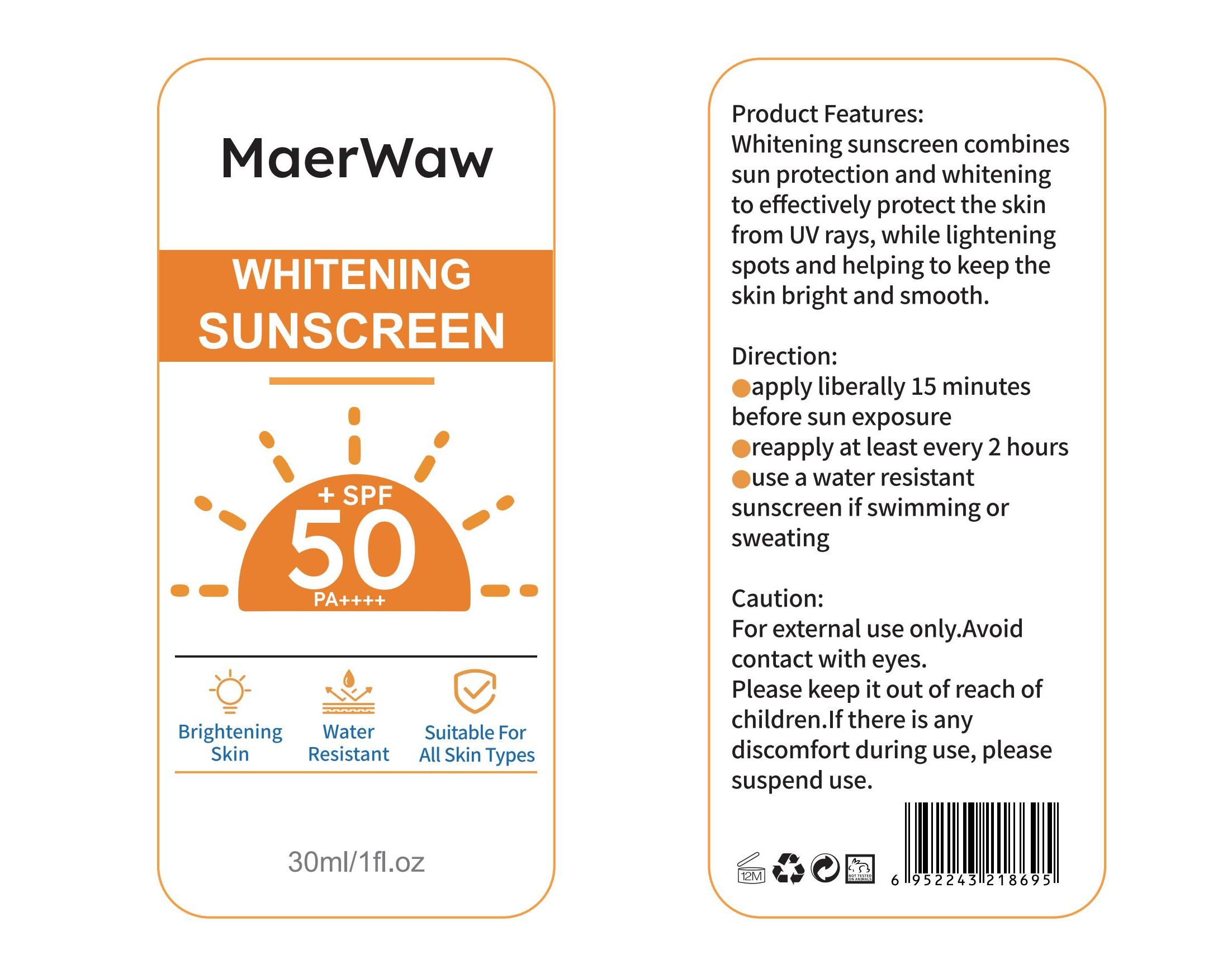 DRUG LABEL: MaerWaw WHITENING SUNSCREEN
NDC: 83566-601 | Form: EMULSION
Manufacturer: Guangdong Aimu Biological Technology Co., Ltd
Category: otc | Type: HUMAN OTC DRUG LABEL
Date: 20240509

ACTIVE INGREDIENTS: TITANIUM DIOXIDE 1.5 g/30 mL; ZINC OXIDE 1.5 g/30 mL; NIACINAMIDE 0.6 g/30 mL; ASCORBIC ACID 0.6 g/30 mL
INACTIVE INGREDIENTS: ALLANTOIN; ALKYL (C12-15) BENZOATE; DIMETHICONE; ALOE FEROX LEAF; PROPYLENE GLYCOL; .ALPHA.-BISABOLOL, (+/-)-; CENTELLA ASIATICA ROOT; MACADAMIA OIL; CETOSTEARYL ALCOHOL; CETEARYL GLUCOSIDE; WHEAT GERM; YEAST .BETA.-D-GLUCAN; GLYCYRRHIZINATE DIPOTASSIUM; ETHYLHEXYLGLYCERIN; TREHALOSE; HYALURONATE SODIUM; MEADOWFOAM SEED OIL; OCTISALATE; CHLORPHENESIN; WATER; WHEAT GERM OIL; CETEARETH-17; PAEONIA LACTIFLORA ROOT; GLYCERIN; ALPHA-TOCOPHEROL ACETATE; XANTHAN GUM; VANILLIN

MaerWaw WHITENING SUNSCREEN

ACTIVE INGREDIENT

Titanium Dioxide
Zinc Oxide
Ascorbic Acid
Niacinamide

PURPOSE

Sunscreen

KEEP OUT OF REACH OF CHILDREN SECTION

INDICATIONS AND USAGE

Whitening sunscreen combines sun protection andwhitening to effectively protect the skin from UV rays, while lightening spots and helping to keep theskin bright and smooth.

WARNINGS

For external use only.

DOSAGE AND ADMINISTRATION

apply liberally 15 minutes before sun exposure.
reapply at least every 2 hours.
use a water resistant sunscreen if swimming or sweating.

STORAGE AND HANDLING

Seal the product and avoid light, store in a cool anddry place.

INACTIVE INGREDIENT

Water
Propylene Glycol
Glycerin
Trehalose
Allantoin
Sodium Hyaluronate
Dipotassium Glycyrrhizate
Limnanthes Alba(Meadowfoam) Seed Oil
Macadamia Ternifolia Seed Oil
Triticum Vulgare (Wheat) Germ Oil
Ethylhexyl Salicylate
C12-15 Alkyl Benzoate
Cetearyl Alcohol
Cetearyl Glucoside
Ceteareth-21
Dimethicone
Tocopheryl Acetate
Bisabolol
Xanthan Gum
Ethylhexylglycerin
Chlorphenesin
Hydrolyzed Beta-Glucan
Paeonia Albiflora Root Extract
Triticum Vulgare(Wheat) Germ Extract
Centella Asiatica Root Extract
Aloe Ferox Leaf Extract